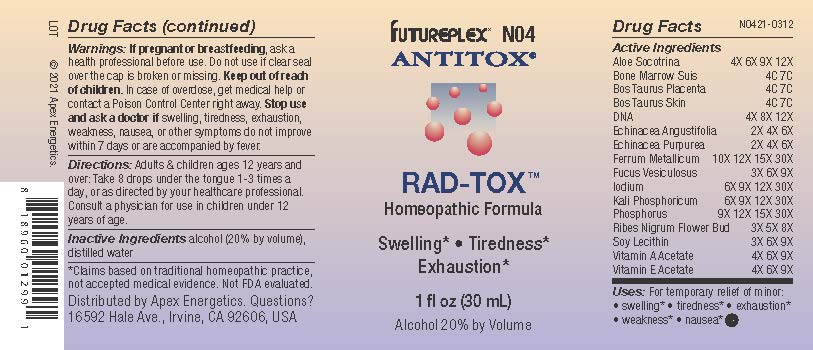 DRUG LABEL: N04
NDC: 63479-1404 | Form: SOLUTION/ DROPS
Manufacturer: Apex Energetics Inc.
Category: homeopathic | Type: HUMAN OTC DRUG LABEL
Date: 20240108

ACTIVE INGREDIENTS: HERRING SPERM DNA 12 [hp_X]/1 mL; BOS TAURUS PLACENTA 7 [hp_C]/1 mL; IRON 30 [hp_X]/1 mL; IODINE 30 [hp_X]/1 mL; DIBASIC POTASSIUM PHOSPHATE 30 [hp_X]/1 mL; PHOSPHORUS 30 [hp_X]/1 mL; RIBES NIGRUM FLOWER BUD 8 [hp_X]/1 mL; LECITHIN, SOYBEAN 9 [hp_X]/1 mL; ALOE 12 [hp_X]/1 mL; SUS SCROFA BONE MARROW 7 [hp_C]/1 mL; ECHINACEA ANGUSTIFOLIA 6 [hp_X]/1 mL; ECHINACEA PURPUREA 6 [hp_X]/1 mL; BOS TAURUS SKIN 7 [hp_C]/1 mL; FUCUS VESICULOSUS 9 [hp_X]/1 mL; VITAMIN A ACETATE 9 [hp_X]/1 mL; .ALPHA.-TOCOPHEROL ACETATE 9 [hp_X]/1 mL
INACTIVE INGREDIENTS: ALCOHOL; WATER

N04

Active Ingredients
Aloe Socotrina | 4X 6X 9X 12X
Bone Marrow Suis | 4C 7C
Bos Taurus Placenta | 4C 7C
Bos Taurus Skin | 4C 7C
Dna | 4X 8X 12X
Echinacea Angustifolia | 2X 4X 6X
Echinacea Purpurea | 2X 4X 6X
Ferrum Metallicum | 10X 12X 15X 30X
Fucus Vesiculosus | 3X 6X 9X
Iodium | 6X 9X 12X 30X
Kali Phosphoricum | 6X 9X 12X 30X
Phosphorus | 9X 12X 15X 30X
Ribes Nigrum Flower Bud | 3X 5X 8X
Soy Lecithin | 3X 6X 9X
Vitamin A Acetate | 4X 6X 9X
Vitamin E Acetate | 4X 6X 9X

INDICATIONS AND USAGE

Uses:

For temporary relief of minor:

swelling*

tiredness*

exhaustion*

weakness*

nausea*

*Claims based on traditional homeopathic practice, not accepted medical evidence. Not FDA evaluated.

Warnings:

PREGNANCY OR BREAST FEEDING

If pregnant or breastfeeding, ask a health professional before use.

Do not use if clear seal over the cap is broken or missing.

Keep out of reach of children. In case of overdose, get medical help or contact a Poison Control Center right away.

Stop use and ask a doctor if swelling, tiredness, exhaustion, weakness, nausea, or other symptoms do not improve within 7 days or are accompanied by fever.

Directions:

Adults & children ages 12 years and over: Take 8 drops under the tongue 1-3 times a day, or as directed by your healthcare professional. Consult a physician for use in children under 12 years of age.

Inactive Ingredients

alcohol (20% by volume), distilled water

Distributed by Apex Energetics. Questions?

16592 Hale Ave., Irvine, CA 92606, USA

PACKAGE LABEL

FUTUREPLEX® N04

ANTITOX®

RAD-TOX™

Homeopathic Formula

Swelling*

Tiredness*

Exhaustion*

1 fl oz (30 mL)

Alcohol 20% by Volume